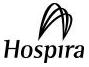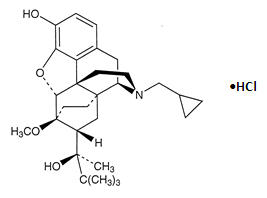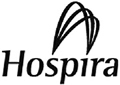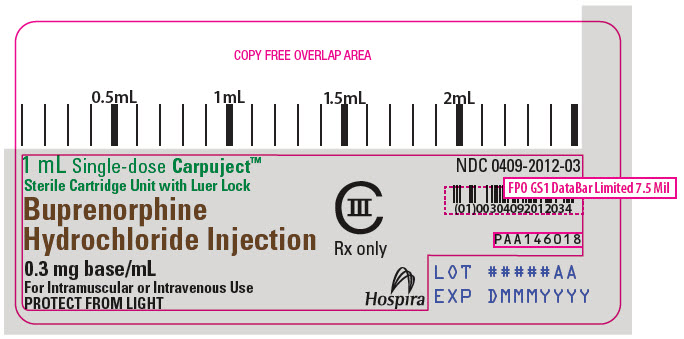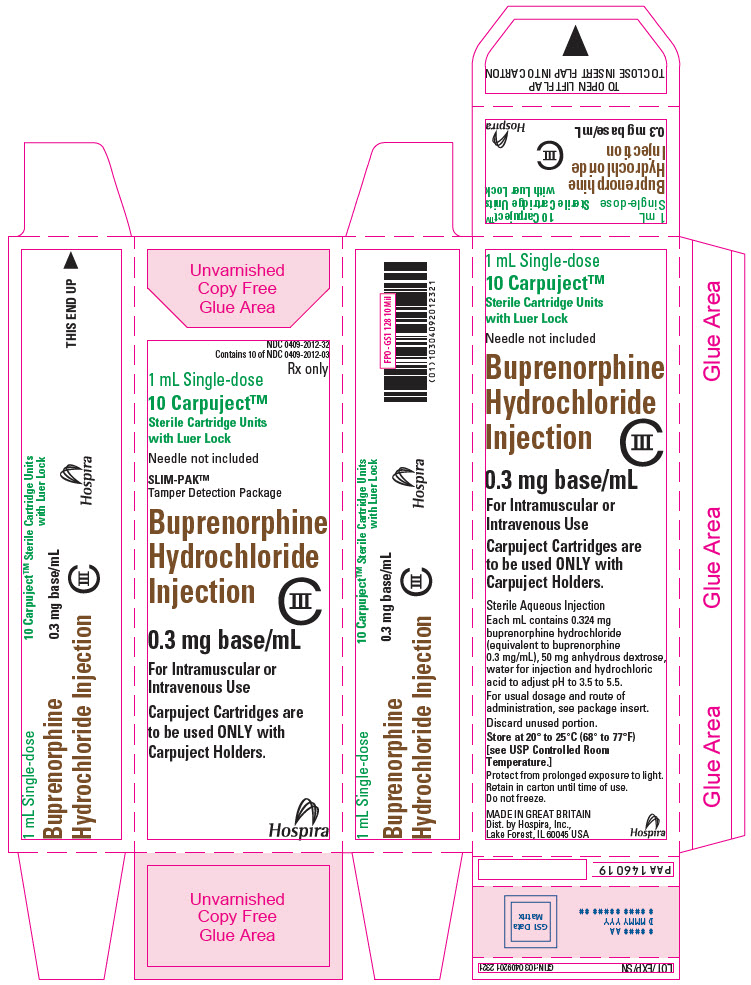 DRUG LABEL: Buprenorphine Hydrochloride
NDC: 0409-2012 | Form: INJECTION, SOLUTION
Manufacturer: Hospira, Inc.
Category: prescription | Type: HUMAN PRESCRIPTION DRUG LABEL
Date: 20251231
DEA Schedule: CIII

ACTIVE INGREDIENTS: BUPRENORPHINE HYDROCHLORIDE 0.3 mg/1 mL
INACTIVE INGREDIENTS: ANHYDROUS DEXTROSE 50 mg/1 mL; WATER; HYDROCHLORIC ACID

Buprenorphine
Hydrochloride
Injection, for intravenous or intramuscular administration

CIII

Rx only

WARNING: SERIOUS AND LIFE-THREATENING RISKS FROM USE OF BUPRENORPHINE HYDROCHLORIDE INJECTION

Addiction, Abuse, and Misuse

Because the use of buprenorphine exposes patients and other users to the risks of opioid addiction, abuse, and misuse, which can lead to overdose and death, assess each patient's risk prior to prescribing and reassess all patients regularly for the development of these behaviors and conditions [see WARNINGS].

Life-Threatening Respiratory Depression

Serious, life-threatening, or fatal respiratory depression may occur with use of buprenorphine, especially during initiation or following a dosage increase. To reduce the risk of respiratory depression, proper dosing and titration of buprenorphine are essential [see WARNINGS].

Risks from Concomitant Use with Benzodiazepines or Other CNS Depressants

Concomitant use of opioids with benzodiazepines or other central nervous system (CNS) depressants, including alcohol, may result in profound sedation, respiratory depression, coma, and death.

Reserve concomitant prescribing of buprenorphine and benzodiazepines or other CNS depressants for use in patients for whom alternative treatment options are inadequate [see WARNINGS, PRECAUTIONS].

Neonatal Opioid Withdrawal Syndrome (NOWS)

Advise pregnant women using opioids for an extended period of time of the risk of Neonatal Opioid Withdrawal Syndrome, which may be life-threatening if not recognized and treated. Ensure that management by neonatology experts will be available at delivery [see WARNINGS].

DESCRIPTION

Buprenorphine hydrochloride is a partial opioid agonist.

The chemical name of buprenorphine hydrochloride is 17-(cyclopropylmethyl)-α-(1,1-dimethylethyl)-4,5-epoxy 18,19-dihydro-3-hydroxy-6-methoxy-α-methyl-6,14-ethenomorphinan-7-methanol, hydrochloride [5α, 7α(S)].

Buprenorphine hydrochloride is a white powder, weakly acidic and with limited solubility in water.

Buprenorphine hydrochloride injection is a clear, sterile, injectable agonist-antagonist analgesic intended for intravenous or intramuscular administration. Each mL of buprenorphine hydrochloride injection contains 0.324 mg buprenorphine hydrochloride (equivalent to 0.3 mg buprenorphine), 50 mg anhydrous dextrose, water for injection and HCl to adjust pH to 3.5 to 5.5.

Buprenorphine hydrochloride has the molecular formula, C29H41NO4∙HCl and the molecular weight of 504.09. It has the following structural formula:

CLINICAL PHARMACOLOGY

Mechanism of Action

Buprenorphine is a partial agonist at the mu-opioid receptor and an antagonist at the kappa-opioid receptor. One unusual property of buprenorphine hydrochloride observed in vitro studies is its very slow rate of dissociation from its receptor. This could account for its longer duration of action than morphine, the unpredictability of its reversal by opioid antagonists, including overdose reversal agent such as naloxone or nalmefene, and its low level of manifest physical dependence.

Pharmacodynamics

Buprenorphine hydrochloride is a parenteral opioid analgesic with 0.3 mg buprenorphine being approximately equivalent to 10 mg morphine sulfate in analgesic and respiratory depressant effects in adults. Pharmacological effects occur as soon as 15 minutes after intramuscular injection and persist for 6 hours or longer. Peak pharmacologic effects usually are observed at 1 hour. When used intravenously, the times to onset and peak effect are shortened.

Buprenorphine demonstrates narcotic antagonist activity and has been shown to be equipotent with naloxone as an antagonist of morphine in the mouse tail flick test.

Effects on the Central Nervous System

The principal action of therapeutic value of buprenorphine is analgesia and is thought to be due to buprenorphine binding with high affinity to opioid receptors on neurons in the brain and spinal cord.

Buprenorphine produces respiratory depression by direct action on brain stem respiratory centers. The respiratory depression involves a reduction in the responsiveness of the brain stem respiratory centers to both increases in carbon dioxide tension and electrical stimulation.

Under usual conditions of use in adults, both buprenorphine hydrochloride and morphine show similar dose-related respiratory depressant effects. At adult therapeutic doses, buprenorphine hydrochloride (0.3 mg buprenorphine) can decrease respiratory rate in an equivalent manner to an equianalgesic dose of morphine (10 mg) [see WARNINGS].

Buprenorphine causes miosis, even in total darkness. Pinpoint pupils are a sign of opioid overdose but are not pathognomonic (e.g., pontine lesions of hemorrhagic or ischemic origins may produce similar findings). Marked mydriasis rather than miosis may be seen due to hypoxia in overdose situations.

Effects on the Gastrointestinal Tract and Other Smooth Muscle

Buprenorphine causes a reduction in motility associated with an increase in smooth muscle tone in the antrum of the stomach and duodenum. Digestion of food in the small intestine is delayed and propulsive contractions are decreased. Propulsive peristaltic waves in the colon are decreased, while tone is increased to the point of spasm, resulting in constipation. Other opioid-induced effects may include a reduction in biliary and pancreatic secretions, spasm of sphincter of Oddi, transient elevations in serum amylase, and opioid-induced esophageal dysfunction (OIED).

Effects on the Cardiovascular System

Buprenorphine produces peripheral vasodilation, which may result in orthostatic hypotension or syncope. Manifestations of histamine release and/or peripheral vasodilation may include pruritus, flushing, red eyes, sweating, and/or orthostatic hypotension.

Buprenorphine hydrochloride may cause a decrease or, rarely, an increase in pulse rate and blood pressure in some patients.

Thorough QT studies with buprenorphine products have demonstrated QT prolongation ≤ 15 msec.

Effects on the Endocrine System

Opioids inhibit the secretion of adrenocorticotropic hormone (ACTH), cortisol, and luteinizing hormone (LH) in humans. They also stimulate prolactin, growth hormone (GH) secretion, and pancreatic secretion of insulin and glucagon.

Use of opioids for an extended period of time may influence the hypothalamic-pituitary-gonadal axis, leading to androgen deficiency that may manifest as low libido, impotence, erectile dysfunction, amenorrhea, or infertility. The causal role of opioids in the clinical syndrome of hypogonadism is unknown because the various medical, physical, lifestyle, and psychological stressors that may influence gonadal hormone levels have not been adequately controlled for in studies conducted to date.

Effects on the Immune System

Opioids have been shown to have a variety of effects on components of the immune system in in vitro and animal models. The clinical significance of these findings is unknown. Overall, the effects of opioids appear to be modestly immunosuppressive.

Concentration–Efficacy Relationships

The minimum effective analgesic concentration will vary widely among patients, especially among patients who have been previously treated with opioid agonists. The minimum effective analgesic concentration of buprenorphine for any individual patient may increase over time due to an increase in pain, the development of a new pain syndrome, and/or the development of analgesic tolerance.

Concentration–Adverse Reaction Relationships

There is a relationship between increasing buprenorphine plasma concentration and increasing frequency of dose-related opioid adverse reactions such as nausea, vomiting, CNS effects, and respiratory depression. In opioid-tolerant patients, the situation may be altered by the development of tolerance to opioid-related adverse reactions.

Pharmacokinetics

The limits of sensitivity of available analytical methodology precluded demonstration of bioequivalence between intramuscular and intravenous routes of administration.

Elimination

In postoperative adults, pharmacokinetic studies have shown elimination half-lives ranging from 1.2 to 7.2 hours (mean 2.2 hours) after intravenous administration of 0.3 mg of buprenorphine. A single, ten-patient, pharmacokinetic study of doses of 3μg/kg in children (age 5 to 7 years) showed a high inter-patient variability, but suggests that the clearance of the drug may be higher in children than in adults. This is supported by at least one repeat-dose study in postoperative pain that showed an optimal inter-dose interval of 4 to 5 hours in pediatric patients as opposed to the recommended 6 to 8 hours in adults.

Metabolism

Buprenorphine undergoes both N-dealkylation to norbuprenorphine and glucuronidation. The N-dealkylation pathway is mediated primarily by CYP3A4. Norbuprenorphine, the major metabolite, can further undergo glucuronidation. Its clearance is related to hepatic blood flow. Studies in patients anesthetized with 0.5% halothane have shown that this anesthetic decreases hepatic blood flow by about 30%.

INDICATIONS AND USAGE

Buprenorphine hydrochloride injection is indicated for the management of pain severe enough to require an opioid analgesic and for which alternate treatments are inadequate.

Limitations of Use:

Because of the risks of addiction, abuse, misuse, overdose, and death, which can occur at any dosage or duration and persist over the course of therapy [see WARNINGS], reserve opioid analgesics, including buprenorphine hydrochloride, for use in patients for whom alternative treatment options are ineffective, not tolerated, or would be otherwise inadequate to provide sufficient management of pain.

CONTRAINDICATIONS

Buprenorphine hydrochloride is contraindicated in patients with:

- Significant respiratory depression [see WARNINGS].
- Acute or severe bronchial asthma in an unmonitored setting or in the absence of resuscitative equipment [see WARNINGS].
- Known or suspected gastrointestinal obstruction, including paralytic ileus [see WARNINGS].
- Hypersensitivity to buprenorphine (e.g., anaphylaxis) or any other ingredient in buprenorphine hydrochloride [see WARNINGS].

WARNINGS

Addiction, Abuse, and Misuse

Buprenorphine hydrochloride contains buprenorphine, a Schedule III controlled substance. As an opioid, buprenorphine hydrochloride exposes users to the risks of addiction, abuse, and misuse.

Although the risk of addiction in any individual is unknown, it can occur in patients appropriately prescribed buprenorphine hydrochloride. Addiction can occur at recommended doses and if the drug is misused or abused. The risk of opioid-related overdose or overdose-related death is increased with higher opioid doses, and this risk persists over the course of therapy. In postmarketing studies, addiction, abuse, misuse, and fatal and non-fatal opioid overdose were observed in patients with long-term opioid use [see ADVERSE REACTIONS].

Assess each patient's risk for opioid addiction, abuse, or misuse prior to prescribing buprenorphine hydrochloride, and reassess all patients receiving buprenorphine hydrochloride for the development of these behaviors and conditions. Risks are increased in patients with a personal or family history of substance abuse (including drug or alcohol addiction or abuse) or mental illness (e.g., major depression). The potential for these risks should not, however, prevent the prescribing of buprenorphine hydrochloride for the proper management of pain in any given patient. Patients at increased risk may be prescribed opioids such as buprenorphine hydrochloride, but use in such patients necessitates intensive counseling about the risks and proper use of buprenorphine hydrochloride along with frequent reevaluation for signs of addiction, abuse, and misuse.

Opioids are sought for nonmedical use and are subject to diversion from legitimate prescribed use. Consider these risks when prescribing or dispensing buprenorphine hydrochloride. Strategies to reduce these risks include proper product storage and control practices for a C-III drug.

Contact local state professional licensing board or state controlled substances authority for information on how to prevent and detect abuse or diversion of this product.

Life-Threatening Respiratory Depression

Serious, life-threatening, or fatal respiratory depression has been reported with the use of opioids, even when used as recommended. Respiratory depression, if not immediately recognized and treated, may lead to respiratory depression and death. Management of respiratory depression may include close observation, supportive measures, and use of opioid overdose reversal agents (e.g., naloxone, nalmefene), depending on the patient's clinical status [see OVERDOSAGE]. Carbon dioxide (CO2) retention from opioid-induced respiratory depression can exacerbate the sedating effects of opioids.

While serious, life-threatening, or fatal respiratory depression can occur at any time during the use of buprenorphine hydrochloride, the risk is greatest during the initiation of therapy or following a dosage increase.

To reduce the risk of respiratory depression, proper dosing and titration of buprenorphine hydrochloride are essential. Overestimating the buprenorphine hydrochloride dosage when converting patients from another opioid product can result in a fatal overdose with the first dose.

Opioids can cause sleep-related breathing disorders including central sleep apnea (CSA) and sleep-related hypoxemia. Opioid use increases the risk of CSA in a dose-dependent fashion. In patients who present with CSA, consider decreasing the opioid dosage using best practices for opioid taper [see DOSAGE AND ADMINISTRATION].

Risks from Concomitant Use with Benzodiazepines or Other CNS Depressants

Profound sedation, respiratory depression, coma, and death may result from the concomitant use of buprenorphine hydrochloride with benzodiazepines and/or other CNS depressants, including alcohol (e.g., non-benzodiazepine sedatives/hypnotics, anxiolytics, tranquilizers, muscle relaxants, general anesthetics, antipsychotics, gabapentinoids [gabapentin or pregabalin], and other opioids). Because of these risks, reserve concomitant prescribing of these drugs for use in patients for whom alternative treatment options are inadequate.

Observational studies have demonstrated that concomitant use of opioid analgesics and benzodiazepines increases the risk of drug-related mortality compared to use of opioid analgesics alone. Because of similar pharmacological properties, it is reasonable to expect similar risk with the concomitant use of other CNS depressant drugs with opioid analgesics [see Drug Interactions].

If the decision is made to prescribe a benzodiazepine or other CNS depressant concomitantly with an opioid analgesic, prescribe the lowest effective dosages and minimum durations of concomitant use. In patients already receiving an opioid analgesic, prescribe a lower initial dose of the benzodiazepine or other CNS depressant than indicated in the absence of an opioid, and titrate based on clinical response. If an opioid analgesic is initiated in a patient already taking a benzodiazepine or other CNS depressant, prescribe a lower initial dose of the opioid analgesic, and titrate based on clinical response. Monitor patients closely for signs and symptoms of respiratory depression and sedation.

Neonatal Opioid Withdrawal Syndrome

Use of buprenorphine hydrochloride for an extended period of time during pregnancy can result in withdrawal in the neonate. Neonatal opioid withdrawal syndrome, unlike opioid withdrawal syndrome in adults, may be life-threatening if not recognized and treated, and requires management according to protocols developed by neonatology experts. Observe newborns for signs of neonatal opioid withdrawal syndrome and manage accordingly. Advise pregnant women using opioids for an extended period of time of the risk of neonatal opioid withdrawal syndrome and ensure that management by neonatology experts will be available at delivery [see WARNINGS, PRECAUTIONS: Information for Patients, Pregnancy].

Opioid-Induced Hyperalgesia and Allodynia

Opioid-Induced Hyperalgesia (OIH) occurs when an opioid analgesic paradoxically causes an increase in pain, or an increase in sensitivity to pain. This condition differs from tolerance, which is the need for increasing doses of opioids to maintain a defined effect [see DEPENDENCE]. Symptoms of OIH include (but may not be limited to) increased levels of pain upon opioid dosage increase, decreased levels of pain upon opioid dosage decrease, or pain from ordinarily non-painful stimuli (allodynia). These symptoms may suggest OIH only if there is no evidence of underlying disease progression, opioid tolerance, opioid withdrawal, or addictive behavior.

Cases of OIH have been reported, both with short-term and longer-term use of opioid analgesics. Though the mechanism of OIH is not fully understood, multiple biochemical pathways have been implicated. Medical literature suggests a strong biologic plausibility between opioid analgesics and OIH and allodynia. If a patient is suspected to be experiencing OIH, carefully consider appropriately decreasing the dose of the current opioid analgesic or opioid rotation (safely switching the patient to a different opioid moiety) [see DOSAGE AND ADMINISTRATION, WARNINGS].

Life-Threatening Respiratory Depression in Patients with Chronic Pulmonary Disease or in Elderly, Cachectic, or Debilitated Patients

The use of buprenorphine hydrochloride in patients with acute or severe bronchial asthma in an unmonitored setting or in the absence of resuscitative equipment is contraindicated.

Patients with Chronic Pulmonary Disease: Buprenorphine hydrochloride-treated patients with significant chronic obstructive pulmonary disease or cor pulmonale, and those with substantially decreased respiratory reserve, hypoxia, hypercapnia, or pre-existing respiratory depression are at increased risk of decreased respiratory drive, including apnea, even at recommended dosages of buprenorphine hydrochloride [see WARNINGS].

Elderly, Cachectic, or Debilitated Patients: Life-threatening respiratory depression is more likely to occur in elderly, cachectic, or debilitated patients as they may have altered pharmacokinetics or altered clearance compared to younger, healthier patients.

Monitor such patients closely, particularly when initiating and titrating buprenorphine hydrochloride and when buprenorphine hydrochloride is given concomitantly with other drugs that depress respiration [see WARNINGS]. Alternatively, consider the use of non-opioid analgesics in these patients.

Adrenal Insufficiency

Cases of adrenal insufficiency have been reported with opioid use, more often following greater than one month of use. Presentation of adrenal insufficiency may include non-specific symptoms and signs including nausea, vomiting, anorexia, fatigue, weakness, dizziness, and low blood pressure. If adrenal insufficiency is suspected, confirm the diagnosis with diagnostic testing as soon as possible. If adrenal insufficiency is diagnosed, treat with physiologic replacement doses of corticosteroids. Wean the patient off of the opioid to allow adrenal function to recover and continue corticosteroid treatment until adrenal function recovers. Other opioids may be tried as some cases reported use of a different opioid without recurrence of adrenal insufficiency. The information available does not identify any particular opioids as being more likely to be associated with adrenal insufficiency.

Severe Hypotension

Buprenorphine hydrochloride may cause severe hypotension including orthostatic hypotension and syncope in ambulatory patients. There is increased risk in patients whose ability to maintain blood pressure has already been compromised by a reduced blood volume, or concurrent administration of certain CNS depressant drugs (e.g., phenothiazines or general anesthetics). Monitor these patients for signs of hypotension after initiating or titrating the dosage of buprenorphine hydrochloride. In patients with circulatory shock, buprenorphine hydrochloride may cause vasodilation that can further reduce cardiac output and blood pressure.

Avoid the use of buprenorphine hydrochloride in patients with circulatory shock.

Risks of Use in Patients with Increased Intracranial Pressure, Brain Tumors, Head Injury, or Impaired Consciousness

In patients who may be susceptible to the intracranial effects of CO2 retention (e.g., those with evidence of increased intracranial pressure or brain tumors), buprenorphine hydrochloride may reduce respiratory drive, and the resultant CO2 retention can further increase intracranial pressure. Monitor such patients for signs of sedation and respiratory depression, particularly when initiating therapy with buprenorphine hydrochloride.

Opioids may also obscure the clinical course in a patient with a head injury.

Avoid the use of buprenorphine hydrochloride in patients with impaired consciousness or coma.

QTc Prolongation

Thorough QT studies with buprenorphine products have demonstrated QT prolongation ≤ 15 msec. This QTc prolongation effect does not appear to be mediated by hERG channels. Based on these two findings, buprenorphine is unlikely to be pro‐arrhythmic when used alone in patients without risk factors. The risk of combining buprenorphine with other QT‐prolonging agents is not known.

Consider these observations in clinical decisions when prescribing buprenorphine hydrochloride to patients with risk factors such as hypokalemia, bradycardia, recent conversion from atrial fibrillation, congestive heart failure, digitalis therapy, baseline QT prolongation, subclinical long‐QT syndrome, or severe hypomagnesemia.

Anaphylactic/Allergic Reactions

Cases of acute and chronic hypersensitivity to buprenorphine have been reported both in clinical trials and in post-marketing experience. The most common signs and symptoms include rashes, hives, and pruritus. Cases of bronchospasm, angioneurotic edema, and anaphylactic shock have been reported. Buprenorphine hydrochloride is contraindicated in patients with a history of hypersensitivity to buprenorphine.

Risk of Gastrointestinal Complications

Buprenorphine hydrochloride is contraindicated in patients with known or suspected gastrointestinal obstruction, including paralytic ileus.

The buprenorphine in buprenorphine hydrochloride may cause spasm of the sphincter of Oddi. Opioids may cause increases in the serum amylase. Monitor patients with biliary tract disease, including acute pancreatitis, for worsening symptoms.

Cases of opioid-induced esophageal dysfunction (OIED) have been reported in patients taking opioids. The risk of OIED may increase as the dose and/or duration of opioids increases. Regularly evaluate patients for signs and symptoms of OIED (e.g., dysphagia, regurgitation, non-cardiac chest pain) and, if necessary, adjust opioid therapy as clinically appropriate [see CLINICAL PHARMACOLOGY].

Increased Risk of Seizures in Patients with Seizure Disorders

The buprenorphine in buprenorphine hydrochloride may increase the frequency of seizures in patients with seizure disorders, and may increase the risk of seizures in other clinical settings associated with seizures. Monitor patients with a history of seizure disorders for worsened seizure control during buprenorphine hydrochloride therapy.

Risks Driving and Operating Machinery

Buprenorphine hydrochloride may impair the mental or physical abilities needed to perform potentially hazardous activities such as driving a car or operating machinery. Warn patients not to drive or operate dangerous machinery unless they are tolerant to the effects of buprenorphine hydrochloride and know how they will react to the medication [see PRECAUTIONS: Information for Patients].

PRECAUTIONS

General: Buprenorphine hydrochloride should be administered with caution in the elderly, debilitated patients, in children and those with severe impairment of hepatic, pulmonary, or renal function; myxedema or hypothyroidism; adrenal cortical insufficiency (e.g., Addison’s disease); CNS depression or coma; toxic psychoses; prostatic hypertrophy or urethral stricture; acute alcoholism; delirium tremens; or kyphoscoliosis.

Because buprenorphine is metabolized by the liver, the activity of buprenorphine may be increased and/or extended in those individuals with impaired hepatic function or those receiving other agents known to decrease hepatic clearance.

Buprenorphine has been shown to increase intracholedochal pressure to a similar degree as other opioid analgesics, and thus should be administered with caution to patients with dysfunction of the biliary tract.

Information for Patients

Addiction, Abuse, and Misuse

Inform patients that the use of buprenorphine hydrochloride, even when taken as recommended, can result in addiction, abuse, and misuse, which can lead to overdose or death [see WARNINGS].

Life-Threatening Respiratory Depression

Inform patients of the risk of life-threatening respiratory depression, including information that the risk is greatest when starting buprenorphine hydrochloride or when the dosage is increased, and that it can occur even at recommended dosages [see WARNINGS].

Hyperalgesia and Allodynia

Advise patients to inform their healthcare provider if they experience symptoms of hyperalgesia, including worsening pain, increased sensitivity to pain, or new pain [see WARNINGS, ADVERSE REACTIONS].

Serotonin Syndrome

Inform patients that opioids could cause a rare but potentially life-threatening condition called serotonin syndrome resulting from concomitant administration of serotonergic drugs. Warn patients of the symptoms of serotonin syndrome and to seek medical attention right away if symptoms develop after discharge from the hospital. Instruct patients to inform their healthcare providers if they are taking, or plan to take serotonergic medications [see PRECAUTIONS; Drug Interactions].

Constipation

Advise patients of the potential for severe constipation, including management instructions and when to seek medical attention [see CLINICAL PHARMACOLOGY: Pharmacodynamics, ADVERSE REACTIONS].

Drug Interactions

Clinically significant drug interactions with Buprenorphine Hydrochloride

Benzodiazepines and Other Central Nervous System (CNS) Depressants
Clinical Impact: | Due to additive pharmacologic effect, the concomitant use of benzodiazepines or other CNS depressants, including alcohol, can increase the risk of hypotension, respiratory depression, profound sedation, coma, and death.
Intervention: | Reserve concomitant prescribing of these drugs for use in patients for whom alternative treatment options are inadequate. Limit dosages and durations to the minimum required. Monitor patients closely for signs of respiratory depression and sedation [see WARNINGS].
Examples: | Benzodiazepines and other sedatives/hypnotics, anxiolytics, tranquilizers, muscle relaxants, general anesthetics, antipsychotics, gabapentinoids (gabapentin or pregabalin), other opioids, alcohol.
Inhibitors of CYP3A4
Clinical Impact: | The concomitant use of buprenorphine and CYP3A4 inhibitors can increase the plasma concentration of buprenorphine, resulting in increased or prolonged opioid effects, particularly when an inhibitor is added after a stable dose of buprenorphine hydrochloride is achieved.; After stopping a CYP3A4 inhibitor, as the effects of the inhibitor decline, the buprenorphine plasma concentration will decrease [see CLINICAL PHARMACOLOGY: Pharmacokinetics], potentially resulting in decreased opioid efficacy or a withdrawal syndrome in patients who had developed physical dependence to buprenorphine.
Intervention: | If concomitant use is necessary, consider dosage reduction of buprenorphine hydrochloride until stable drug effects are achieved. Monitor patients for respiratory depression and sedation.; If a CYP3A4 inhibitor is discontinued, consider increasing the buprenorphine hydrochloride dosage until stable drug effects are achieved. Monitor for signs of opioid withdrawal.
Examples: | Macrolide antibiotics (e.g., erythromycin), azole-antifungal agents (e.g., ketoconazole), protease inhibitors (e.g., ritonavir).
CYP3A4 Inducers
Clinical Impact: | The concomitant use of buprenorphine and CYP3A4 inducers can decrease the plasma concentration of buprenorphine [see CLINICAL PHARMACOLOGY: Pharmacokinetics], potentially resulting in decreased efficacy or onset of a withdrawal syndrome in patients who have developed physical dependence to buprenorphine.; After stopping a CYP3A4 inducer, as the effects of the inducer decline, the buprenorphine plasma concentration will increase [see CLINICAL PHARMACOLOGY: Pharmacokinetics], which could increase or prolong both therapeutic effects and adverse reactions and may cause serious respiratory depression.
Intervention: | If concomitant use is necessary, consider increasing the buprenorphine hydrochloride dosage until stable drug effects are achieved. Monitor for signs of opioid withdrawal.; If a CYP3A4 inducer is discontinued, consider buprenorphine hydrochloride dosage reduction and monitor for signs of respiratory depression and sedation.
Examples: | Rifampin, carbamazepine, phenytoin
Serotonergic Drugs
Clinical Impact: | The concomitant use of opioids with other drugs that affect the serotonergic neurotransmitter system has resulted in serotonin syndrome.
Intervention: | If concomitant use is warranted, carefully observe the patient, particularly during treatment initiation and dose adjustment. Discontinue buprenorphine hydrochloride if serotonin syndrome is suspected.
Examples: | Selective serotonin reuptake inhibitors (SSRIs), serotonin and norepinephrine reuptake inhibitors (SNRIs), tricyclic antidepressants (TCAs), triptans, 5-HT3 receptor antagonists, drugs that affect the serotonin neurotransmitter system (e.g., mirtazapine, trazodone, tramadol), certain muscle relaxants (i.e., cyclobenzaprine, metaxalone), monoamine oxidase (MAO) inhibitors (those intended to treat psychiatric disorders and also others, such as linezolid and intravenous methylene blue).
Monoamine Oxidase Inhibitors (MAOIs)
Clinical Impact: | MAOI interactions with opioids may manifest as serotonin syndrome opioid toxicity (e.g., respiratory depression, coma).
Intervention: | The use of buprenorphine hydrochloride is not recommended for patients taking MAOIs or within 14 days of stopping such treatment.
Examples: | Phenelzine, tranylcypromine, linezolid
Mixed Agonist/Antagonist and Partial Agonist Opioid Analgesics
Clinical Impact: | May reduce the analgesic effect of buprenorphine hydrochloride and/or precipitate withdrawal symptoms.
Intervention: | Avoid concomitant use.
Examples: | Butorphanol, nalbuphine, pentazocine
Muscle Relaxants
Clinical Impact: | Buprenorphine may enhance the neuromuscular blocking action of skeletal muscle relaxants and produce an increased degree of respiratory depression.
Intervention: | Monitor patients for signs of respiratory depression that may be greater than otherwise expected, decrease the dosage of buprenorphine hydrochloride and/or the muscle relaxant as necessary.
Examples: | Cyclobenzaprine, metaxalone.
Diuretics
Clinical Impact: | Opioids can reduce the efficacy of diuretics by inducing the release of antidiuretic hormone.
Intervention: | Monitor patients for signs of diminished diuresis and/or effects on blood pressure and increase the dosage of the diuretic as needed.
Anticholinergic Drugs
Clinical Impact: | The concomitant use of anticholinergic drugs may increase the risk of urinary retention and/or severe constipation, which may lead to paralytic ileus.
Intervention: | Monitor patients for signs of urinary retention or reduced gastric motility when buprenorphine hydrochloride is used concomitantly with anticholinergic drugs.
Antiretrovirals: Nucleoside reverse transcriptase inhibitors (NRTIs)
Clinical Impact: | Nucleoside reverse transcriptase inhibitors (NRTIs) do not appear to induce or inhibit the P450 enzyme pathway, thus no interactions with buprenorphine are expected.
Intervention: | None
Antiretrovirals: Non-nucleoside reverse transcriptase inhibitors (NNRTIs)
Clinical Impact: | Non-nucleoside reverse transcriptase inhibitors (NNRTIs) are metabolized principally by CYP3A4. Efavirenz, nevirapine, and etravirine are known CYP3A inducers, whereas delaviridine is a CYP3A inhibitor. Significant pharmacokinetic interactions between NNRTIs (e.g., efavirenz and delavirdine) and buprenorphine have been shown in clinical studies, but these pharmacokinetic interactions did not result in any significant pharmacodynamic effects.
Intervention: | If prescribing an NNRTI to a patient taking buprenorphine hydrochloride, frequently reevaluate for this interaction and adjust dosing as necessary.
Examples: | Efavirenz, nevirapine, etravirine, delavirdine
Antiretrovirals: Protease inhibitors (PIs)
Clinical Impact: | Studies have shown some antiretroviral protease inhibitors (PIs) with CYP3A4 inhibitory activity (nelfinavir, lopinavir/ritonavir, ritonavir) have little effect on buprenorphine pharmacokinetic and no significant pharmacodynamic effects. Other PIs with CYP3A4 inhibitory activity (atazanavir and atazanavir/ritonavir) resulted in elevated levels of buprenorphine and norbuprenorphine, and patients in one study reported increased sedation. Symptoms of opioid excess have been found in post-marketing reports of patients receiving buprenorphine and atazanavir with and without ritonavir concomitantly.
Intervention: | Monitor patients taking buprenorphine hydrochloride and atazanavir with and without ritonavir, and dose reduction of buprenorphine hydrochloride may be warranted.
Examples: | Atazanavir, ritonavir

Carcinogenesis, Mutagenesis and Impairment of Fertility

Carcinogenesis

Carcinogenicity studies were conducted in Sprague-Dawley rats and CD-1 mice. Buprenorphine was administered in the diet at doses of 0.6, 5.5, and 56 mg/kg/day for 27 months in rats. These doses were approximately equivalent to 5.7, 52, and 534 times the recommended human dose (1.2 mg) on a mg/m^2 body surface area basis. Statistically significant dose-related increases in testicular interstitial (Leydig's) cell tumors occurred, according to the trend test adjusted for survival. Pairwise comparison of the high dose against control failed to show statistical significance. In the mouse study, buprenorphine was administered in the diet at doses of 8, 50, and 100 mg/kg/day for 86 weeks.

The high dose was approximately equivalent to 477 times the recommended human dose (1.2 mg) on a mg/m^2 basis. Buprenorphine was not carcinogenic in mice.

Mutagenesis

Buprenorphine was studied in a series of tests. Results were negative in Chinese hamster bone marrow and spermatogonia cells, and negative in mouse lymphoma L5178Y assay. Results were equivocal in the Ames test: negative in studies in two laboratories, but positive in frame shift mutation at high dose (5 mg/plate) in a third study.

Impairment of Fertility

Reproduction studies of buprenorphine in rats demonstrated no evidence of impaired fertility at daily oral doses up to 80 mg/kg (approximately 763 times the recommended human daily dose of 1.2 mg on a mg/m^2 basis) or up to 5 mg/kg intramuscular or subcutaneous (approximately 48 times the recommended human daily dose of 1.2 mg on a mg/m^2 basis).

Pregnancy

Risk Summary

Use of opioid analgesics for an extended period of time during pregnancy may cause neonatal opioid withdrawal syndrome [see WARNINGS: Neonatal Opioid Withdrawal Syndrome]. Available data with buprenorphine hydrochloride in pregnant women are insufficient to inform a drug-associated risk for major birth defects and miscarriage.

Reproductive and developmental studies in rats and rabbits identified adverse events at approximately 2 times the maximum recommended human dose (MRHD) of 1.8 mg/day of buprenorphine hydrochloride. Embryofetal death was observed in both rats and rabbits administered buprenorphine during the period of organogenesis at doses approximately 54 and 2.2 times, respectively, the MRHD of 1.8 mg/day of buprenorphine. Pre-and postnatal development studies in rats demonstrated increased neonatal deaths at 2.7 times and above and dystocia at approximately 27 times the MRHD of 1.8 mg/day of buprenorphine. No clear teratogenic effects were seen when buprenorphine was administered during organogenesis with a range of doses 5 times or greater than the MRHD of 1.8 mg/day of buprenorphine. However, increases in skeletal abnormalities were noted in rats and rabbits administered buprenorphine daily during organogenesis at doses approximately 5.4 and 10.8 times the MRHD of 1.8 mg/day of buprenorphine, respectively. In a few studies, some events such as acephalus and omphalocele were also observed but these findings were not clearly treatment-related [see Data].

Based on animal data, advise pregnant women of the potential risk to a fetus.

The estimated background risk of major birth defects and miscarriage for the indicated population is unknown. All pregnancies have a background risk of birth defect, loss, or other adverse outcomes. In the U.S. general population, the estimated background risk of major birth defects and miscarriage in clinically recognized pregnancies is 2 to 4% and 15 to 20%, respectively.

Clinical Considerations

Fetal/neonatal adverse reactions

Use of opioid analgesics for an extended period of time during pregnancy for medical or nonmedical purposes can result in physical dependence in the neonate and neonatal opioid withdrawal syndrome shortly after birth.

Neonatal opioid withdrawal syndrome presents as irritability, hyperactivity and abnormal sleep pattern, high pitched cry, tremor, vomiting, diarrhea, and/or failure to gain weight. Signs of neonatal withdrawal usually occur in the first days after birth. The duration and severity of neonatal opioid withdrawal syndrome may vary. Observe newborns for signs of neonatal opioid withdrawal syndrome and manage accordingly [see WARNINGS: Neonatal Opioid Withdrawal Syndrome].

Labor and Delivery

The safety of buprenorphine hydrochloride given during labor and delivery has not been established. As with all opioids, use of buprenorphine prior to delivery may result in respiratory depression in the newborn.

Opioids cross the placenta and may produce respiratory depression and psycho-physiologic effects in neonates. An opioid overdose reversal agent, such as naloxone or nalmefene, should be available for reversal of opioid induced respiratory depression in the neonate.

Data

Human Data

Studies have been conducted to evaluate neonatal outcomes in women exposed to buprenorphine during pregnancy. Limited published data on malformations from trials, observational studies, case series, and case reports on buprenorphine use in pregnancy have not shown an increased risk of major malformations. Based on these studies the incidence of neonatal abstinence syndrome is not clear and there does not appear to be a dose-response relationship.

Animal Data

The exposure margins listed below are based on body surface area comparisons (mg/m^2) to MRHD of 1.8 mg buprenorphine via buprenorphine hydrochloride.

Following oral administration to rats no teratogenic effects were observed at buprenorphine doses up to 250 mg/kg/day (estimated exposure approximately 1,351 times the MRHD of 1.8 mg) in the presence of maternal toxicity (mortality). Following oral administration to rabbits, no teratogenic effects were observed at buprenorphine doses up to 40 mg/kg/day (estimated exposure approximately 432 times the MRHD of 1.8 mg) in the absence of clear maternal toxicity.

No definitive drug-related teratogenic effects were observed in rats and rabbits at IM doses up to 30 mg/kg/day (estimated exposure approximately 161 times and 324 times, respectively, the MRHD of 1.8 mg). Maternal toxicity resulting in mortality was noted in these studies in both rats and rabbits. Acephalus was observed in one rabbit fetus from the low-dose group and omphalocele was observed in two rabbit fetuses from the same litter in the mid-dose group; no findings were observed in fetuses from the high-dose group. Maternal toxicity was seen in the high-dose group but not at the lower doses where the findings were observed. Following oral administration of buprenorphine to rats, dose-related post-implantation losses, evidenced by increases in the numbers of early resorptions with consequent reductions in the numbers of fetuses, were observed at doses of 10 mg/kg/day or greater (estimated exposure approximately 54 times the MRHD of 1.8 mg).

In the rabbit, increased post-implantation losses occurred at an oral dose of 40 mg/kg/day. Following IM administration in the rat and the rabbit, post-implantation losses, as evidenced by decreases in live fetuses and increases in resorptions, occurred at 30 mg/kg/day.

Buprenorphine was not teratogenic in rats or rabbits after IM or subcutaneous (SC) doses up to 5 mg/kg/day (estimated exposure was approximately 27 and 54 times, respectively, the MRHD of 1.8 mg), after IV doses up to 0.8 mg/kg/day (estimated exposure was approximately 4.3 and 8.7 times, respectively, the MRHD of 1.8 mg), or after oral doses up to 160 mg/kg/day in rats (estimated exposure was approximately 865 times the MRHD of 1.8 mg) and 25 mg/kg/day in rabbits (estimated exposure was approximately 270 times the MRHD of 1.8 mg). Significant increases in skeletal abnormalities (e.g., extra thoracic vertebra or thoraco-lumbar ribs) were noted in rats after SC administration of 1 mg/kg/day and up (estimated exposure was approximately 5.4 times the MRHD of 1.8 mg), but were not observed at oral doses up to 160 mg/kg/day.

Increases in skeletal abnormalities in rabbits after IM administration of 5 mg/kg/day (estimated exposure was approximately 54 times the MRHD of 1.8 mg) in the absence of maternal toxicity or oral administration of 1 mg/kg/day or greater (estimated exposure was approximately 10.8 times the MRHD of 1.8 mg) were not statistically significant.

In rabbits, buprenorphine produced statistically significant pre-implantation losses at oral doses of 1 mg/kg/day or greater and post-implantation losses that were statistically significant at IV doses of 0.2 mg/kg/day or greater (estimated exposure approximately 2.2 times the MRHD of 1.8 mg). No maternal toxicity was noted at doses causing post-implantation loss in this study.

Dystocia was noted in pregnant rats treated intramuscularly with buprenorphine from Gestation Day 14 through Lactation Day 21 at 5 mg/kg/day (approximately 27 times the MRHD of 1.8 mg).

Fertility, pre-, and post-natal development studies with buprenorphine in rats indicated increases in neonatal mortality after oral doses of 0.8 mg/kg/day and up (approximately 4.3 times the MRHD of 1.8 mg), after IM doses of 0.5 mg/kg/day and up (approximately 2.7 times the MRHD of 1.8 mg), and after SC doses of 0.1 mg/kg/day and up (approximately 0.5 times the MRHD of 1.8 mg). An apparent lack of milk production during these studies likely contributed to the decreased pup viability and lactation indices. Delays in the occurrence of righting reflex and startle response were noted in rat pups at an oral dose of 80 mg/kg/day (approximately 432 times the MRHD of 1.8 mg).

Lactation

Risk Summary

An apparent lack of milk production during general reproduction studies with buprenorphine in rats caused decreased viability and lactation indices. Use of high doses of sublingual buprenorphine in pregnant women showed that buprenorphine passes into the mother's milk.

Clinical Considerations

Breast-feeding is not advised in nursing mothers treated with buprenorphine hydrochloride.

Females and Males of Reproductive Potential

Infertility

Use of opioids for an extended period of time may cause reduced fertility in females and males of reproductive potential. It is not known whether these effects on fertility are reversible [see ADVERSE REACTIONS].

Pediatric Use

The safety and effectiveness of buprenorphine have been established for children between 2 and 12 years of age. Use of buprenorphine in children is supported by evidence from adequate and well-controlled trials of buprenorphine in adults, with additional data from studies of 960 children ranging in age from 9 months to 18 years of age. Data is available from a pharmacokinetic study, several controlled clinical trials, and several large post-marketing studies and case series. The available information provides reasonable evidence that buprenorphine may be used safely in children ranging from 2 to 12 years of age, and that it is of similar effectiveness in children as in adults.

Geriatric Use

Elderly patients (aged 65 years or older) may have increased sensitivity to buprenorphine. In general, use caution when selecting a dosage for an elderly patient, usually starting at the low end of the dosing range, reflecting the greater frequency of decreased hepatic, renal, or cardiac function and of concomitant disease or other drug therapy.

Respiratory depression is the chief risk for elderly patients treated with opioids, and has occurred after large initial doses were administered to patients who were not opioid-tolerant or when opioids were co-administered with other agents that depress respiration. Titrate the dosage of buprenorphine hydrochloride slowly in geriatric patients and monitor for signs of central nervous system and respiratory depression [see WARNINGS, PRECAUTIONS].

Buprenorphine is known to be substantially excreted by the kidney, and the risk of adverse reactions to this drug may be greater in patients with impaired renal function. Because elderly patients are more likely to have decreased renal function, care should be taken in dose selection, and it may be useful to monitor renal function.

ADVERSE REACTIONS

The most frequent side effect in clinical studies involving 1,133 patients was sedation which occurred in approximately two-thirds of the patients. Although sedated, these patients could easily be aroused to an alert state.

Other less frequent adverse reactions occurring in 5 to 10% of the patients were:

 | Nausea | Dizziness/Vertigo

Occurring in 1 to 5% of the patients:

 | Sweating | Headache
 | Hypotension | Nausea/Vomiting
 | Vomiting | Hypoventilation
 | Miosis

The following adverse reactions were reported to have occurred in less than 1% of the patients:

CNS Effect: confusion, blurred vision, euphoria, weakness/fatigue, dry mouth, nervousness, depression, slurred speech, paresthesia.

Cardiovascular: hypertension, tachycardia, bradycardia.

Gastrointestinal: constipation.

Respiratory: dyspnea, cyanosis.

Dermatological: pruritus.

Ophthalmological: diplopia, visual abnormalities.

Miscellaneous: injection site reaction, urinary retention, dreaming, flushing/warmth, chills/cold, tinnitus, conjunctivitis, Wenckebach block, and psychosis.

Other effects observed infrequently include malaise, hallucinations, depersonalization, coma, dyspepsia, flatulence, apnea, rash, amblyopia, tremor, and pallor.

The following reactions have been reported to occur rarely: loss of appetite, dysphoria/agitation, diarrhea, urticaria, and convulsions/lack of muscle coordination.

Allergic Reactions: Cases of acute and chronic hypersensitivity to buprenorphine have been reported both in clinical trials and in the postmarketing experience of buprenorphine and other buprenorphine-containing products. The most common signs and symptoms include rashes, hives, and pruritus. Cases of bronchospasm, angioneurotic edema, and anaphylactic shock have been reported. A history of hypersensitivity to buprenorphine is a contraindication to buprenorphine.

In the United Kingdom, buprenorphine hydrochloride was made available under monitored release regulation during the first year of sale, and yielded data from 1,736 physicians on 9,123 patients (17,120 administrations). Data on 240 children under the age of 18 years were included in this monitored release program. No important new adverse effects attributable to buprenorphine hydrochloride were observed.

Postmarketing Experience

Serotonin syndrome: Cases of serotonin syndrome, a potentially life-threatening condition, have been reported during concomitant use of opioids with serotonergic drugs.

Adrenal insufficiency: Cases of adrenal insufficiency have been reported with opioid use, more often following greater than one month of use.

Androgen deficiency: Cases of androgen deficiency have occurred with use of opioids for an extended period of time [see CLINICAL PHARMACOLOGY: Pharmacodynamics].

Hyperalgesia and Allodynia: Cases of hyperalgesia and allodynia have been reported with opioid therapy of any duration [see WARNINGS].

Hypoglycemia: Cases of hypoglycemia have been reported in patients taking opioids. Most reports were in patients with at least one predisposing risk factor (e.g., diabetes).

Opioid-induced esophageal dysfunction (OIED): Cases of OIED have been reported in patients taking opioids and may occur more frequently in patients taking higher doses of opioids, and/or in patients taking opioids longer term [see WARNINGS].

Adverse Reactions from Observational Studies

A prospective, observational cohort study estimated the risks of addiction, abuse, and misuse in patients initiating long-term use of Schedule II opioid analgesics between 2017 and 2021. Study participants included in one or more analyses had been enrolled in selected insurance plans or health systems for at least one year, were free of at least one outcome at baseline, completed a minimum number of follow-up assessments, and either: 1) filled multiple extended-release/long-acting opioid analgesic prescriptions

during a 90-day period (n=978); or 2) filled any Schedule II opioid analgesic prescriptions covering at least 70 of 90 days (n=1,244). Those included also had no dispensing of the qualifying opioids in the previous 6 months.

Over 12 months:

- approximately 1% to 6% of participants across the two cohorts newly met criteria for addiction, as assessed with two validated interview-based measures of moderate-to-severe opioid use disorder based on Diagnostic and Statistical Manual of Mental Disorders, Fifth Edition (DSM-5) criteria, and
- approximately 9% and 22% of participants across the two cohorts newly met criteria for prescription opioid abuse and misuse [defined in DRUG ABUSE AND DEPENDENCE], respectively, as measured with a validated self-reported instrument.

A retrospective, observational cohort study estimated the risk of opioid-involved overdose or opioid overdose-related death in patients with new long-term use of Schedule II opioid analgesics from 2006 through 2016 (n=220,249). Included patients had been enrolled in either one of two commercial insurance programs, one managed care program, or one Medicaid program for at least 9 months. New long-term use was defined as having Schedule II opioid analgesic prescriptions covering at least 70 days’ supply over the 3 months prior to study entry and none during the preceding 6 months. Patients were excluded if they had an opioid-involved overdose in the 9 months prior to study entry. Overdose was measured using a validated medical code-based algorithm with linkage to the National Death Index database. The 5-year cumulative incidence estimates for opioid-involved overdose or opioid overdose-related death ranged from approximately 1.5% to 4% across study sites, counting only the first event during follow-up. Approximately 17% of first opioid overdoses observed over the entire study period (5-11 years, depending on the study site) were fatal. Higher baseline opioid dose was the strongest and most consistent predictor of opioid-involved overdose or opioid overdose-related death. Study exclusion criteria may have selected patients at lower risk of overdose, and substantial loss to follow-up (approximately 80%) also may have biased estimates.

The risk estimates from the studies described above may not be generalizable to all patients receiving opioid analgesics, such as those with exposures shorter or longer than the duration evaluated in the studies.

DRUG ABUSE AND DEPENDENCE

Controlled Substance

Buprenorphine hydrochloride contains buprenorphine, a Schedule III controlled substance.

Abuse

Buprenorphine hydrochloride contains buprenorphine, a substance with high potential for misuse and abuse, which can lead to the development of substance use disorder, including addiction [see WARNINGS].

Misuse is the intentional use, for therapeutic purposes, of a drug by an individual in a way other than prescribed by a healthcare provider or for whom it was not prescribed.

Abuse is the intentional, non-therapeutic use of a drug, even once, for its desirable psychological or physiological effects.

Drug addiction is a cluster of behavioral, cognitive, and physiological phenomena that may include a strong desire to take the drug, difficulties in controlling drug use (e.g., continuing drug use despite harmful consequences, giving a higher priority to drug use than other activities and obligations), and possible tolerance or physical dependence.

Misuse and abuse of buprenorphine hydrochloride increases risk of overdose, which may lead to central nervous system and respiratory depression, hypotension, seizures, and death. The risk is increased with concurrent abuse of buprenorphine hydrochloride with alcohol and/or other CNS depressants. Abuse of and addiction to opioids in some individuals may not be accompanied by concurrent tolerance and symptoms of physical dependence. In addition, abuse of opioids can occur in the absence of addiction.

All patients treated with opioids require careful and frequent reevaluation for signs of misuse, abuse, and addiction, because use of opioid analgesic products carries the risk of addiction even under appropriate medical use. Patients at high risk of buprenorphine hydrochloride abuse include those with a history of prolonged use of any opioid, including products containing buprenorphine, those with drug or alcohol abuse, or those who use buprenorphine hydrochloride in combination with other abused drugs.

"Drug-seeking" behavior is very common in persons with substance use disorders. Drug-seeking tactics include emergency calls or visits near the end of office hours, refusal to undergo appropriate examination, testing, or referral, repeated "loss" of prescriptions, tampering with prescriptions, and reluctance to provide prior medical records or contact information for other treating healthcare provider(s). "Doctor shopping" (visiting multiple prescribers to obtain additional prescriptions) is common among people who abuse drugs and people with substance use disorder. Preoccupation with achieving adequate pain relief can be appropriate behavior in a patient with inadequate pain control.

Buprenorphine hydrochloride, like other opioids, can be diverted for nonmedical use into illicit channels of distribution. Careful record-keeping of prescribing information, including quantity, frequency, and renewal requests, as required by state and federal law, is strongly advised.

Proper assessment of the patient, proper prescribing practices, periodic reevaluation of therapy, and proper dispensing and storage are appropriate measures that help to limit abuse of opioid drugs.

Risks Specific to Abuse of Buprenorphine Hydrochloride

Abuse of buprenorphine hydrochloride poses a risk of overdose and death. The risk is increased with concurrent abuse of buprenorphine hydrochloride with alcohol and/or other CNS depressants.

Parenteral drug abuse is commonly associated with transmission of infectious diseases such as hepatitis and HIV.

Dependence

Both tolerance and physical dependence can develop during use of opioid therapy. Tolerance is a physiological state characterized by a reduced response to a drug after repeated administration (i.e., a higher dose of a drug is required to produce the same effect that was once obtained at a lower dose).

Physical dependence is a state that develops as a result of a physiological adaptation in response to repeated drug use, manifested by withdrawal signs and symptoms after abrupt discontinuation or a significant dose reduction of a drug.

Withdrawal may be precipitated through the administration of drugs with opioid antagonist activity (e.g., naloxone, nalmefene), mixed agonist/antagonist analgesics (e.g., pentazocine, butorphanol, nalbuphine), or partial agonists (e.g., buprenorphine). Physical dependence may not occur to a clinically significant degree until after several days to weeks of continued use.

Buprenorphine hydrochloride should not be rapidly reduced or abruptly discontinued [see DOSAGE AND ADMINISTRATION]. If buprenorphine hydrochloride is rapidly reduced or abruptly discontinued in a physically-dependent patient, a withdrawal syndrome may occur, typically characterized by restlessness, lacrimation, rhinorrhea, perspiration, chills, myalgia, and mydriasis. Other signs and symptoms also may develop, including irritability, anxiety, backache, joint pain, weakness, abdominal cramps, insomnia, nausea, anorexia, vomiting, diarrhea, or increased blood pressure, respiratory rate, or heart rate.

Infants born to mothers physically-dependent on opioids will also be physically-dependent and may exhibit respiratory difficulties and withdrawal signs [see Pregnancy].

OVERDOSAGE

Clinical Presentation

Acute overdose with buprenorphine can be manifested by respiratory depression, somnolence progressing to stupor or coma, skeletal muscle flaccidity, cold and clammy skin, constricted pupils, and, in some cases, pulmonary edema, bradycardia, hypotension, hypoglycemia, partial or complete airway obstruction, atypical snoring, and death. Marked mydriasis rather than miosis may be seen with hypoxia in overdose situations [see CLINICAL PHARMACOLOGY]. Toxic leukoencephalopathy has been reported after opioid overdose and can present hours, days, or weeks after apparent recovery from the initial intoxication.

Treatment of Overdose

In the case of overdose, priorities are the reestablishment of a patent and protected airway and institution of assisted or controlled ventilation, if needed. Employ other supportive measures (including oxygen and vasopressors) in the management of circulatory shock and pulmonary edema as indicated. Cardiac arrest or arrhythmias will require advanced life-support measures.

For clinically significant respiratory or circulatory depression secondary to buprenorphine overdose, administer an opioid overdose reversal agent such as naloxone or nalmefene.

The healthcare provider must remember that buprenorphine is a long-acting depressant (36 to 48 hours), whereas naloxone acts for much shorter periods (one to three hours). Because the duration of opioid reversal is expected to be less than the duration of action of buprenorphine in buprenorphine hydrochloride, carefully monitor the patient until spontaneous respiration is reliably reestablished. If the response to an opioid overdose reversal agent is suboptimal or only brief in nature, administer additional reversal agent as directed by the product's prescribing information.

In an individual physically-dependent on opioids, the administration of the usual dose of an opioid overdose reversal agent will precipitate an acute withdrawal syndrome. The severity of the withdrawal symptoms experienced will depend on the degree of physical dependence and the dose of the reversal agent administered. If a decision is made to treat serious respiratory depression in the physically-dependent patient, administration of the reversal agent should be initiated with care and by titration with smaller than usual doses of the reversal agent.

DOSAGE AND ADMINISTRATION

- Buprenorphine hydrochloride should be prescribed only by healthcare professionals who are knowledgeable about the use of opioids and how to mitigate the associated risks.
- Use the lowest effective dosage for the shortest duration of time consistent with individual patient treatment goals [see WARNINGS]. Because the risk of overdose increases as opioid doses increase, reserve titration to higher doses of buprenorphine hydrochloride for patients in whom lower doses are insufficiently effective and in whom the expected benefits of using a higher dose opioid clearly outweigh the substantial risks.
- Many acute pain conditions (e.g., the pain that occurs with a number of surgical procedures or acute musculoskeletal injuries) require no more than a few days of an opioid analgesic. Clinical guidelines on opioid prescribing for some acute pain conditions are available.
- There is variability in the opioid analgesic dose and duration needed to adequately manage pain due both to the cause of pain and to individual patient factors. Initiate the dosing regimen for each patient individually, taking into account the patient’s underlying cause and severity of pain, prior analgesic treatment and response, and risk factors for addiction, abuse, and misuse [see WARNINGS].
- Respiratory depression can occur at any time during opioid therapy, especially when initiating and following dosage increases with buprenorphine hydrochloride. Consider this risk when selecting an initial dose and when making dose adjustments [see WARNINGS].
- Inspect buprenorphine hydrochloride injection for particulate matter and discoloration prior to administration.

Dosing

Adults and Pediatric Patients over 12 years of age

The initial starting dose is 1 mL buprenorphine hydrochloride injection (0.3 mg buprenorphine) given by deep intramuscular or slow (over at least 2 minutes) intravenous injection at up to 6-hour intervals, as needed.

Repeat once (up to 0.3 mg) if required, 30 to 60 minutes after initial dosage, giving consideration to previous dose pharmacokinetics, and thereafter only as needed. In high-risk patients (e.g., elderly, debilitated, presence of respiratory disease, etc.) and/or in patients where other CNS depressants are present, such as in the immediate postoperative period, the dose should be limited to the minimum required.

Extra caution should be exercised with the intravenous route of administration, particularly with the initial dose. Occasionally, it may be necessary to administer single doses of up to 0.6 mg to adults depending on the severity of the pain and the response of the patient. This dose should only be given intramuscularly and only to adult patients who are not in a high risk category [see WARNINGS, PRECAUTIONS]. At this time, there are insufficient data to recommend single doses greater than 0.6 mg for long-term use.

Pediatric Patients

Buprenorphine hydrochloride has been used in pediatric patients 2 to 12 years of age at doses between 2 to 6 micrograms/kg of body weight given every 4 to 6 hours. There is insufficient experience to recommend a dose in infants below the age of two years, single doses greater than 6 micrograms/kg of body weight, or the use of a repeat or second dose at 30 to 60 minutes (such as is used in adults). Since there is some evidence that not all pediatric patients clear buprenorphine faster than adults, fixed interval or "round-the-clock" dosing should not be undertaken until the proper inter-dose interval has been established by clinical observation of the child. Healthcare providers should recognize that, as with adults, some pediatric patients may not need to be remedicated for 6 to 8 hours.

Safety and Handling

Buprenorphine hydrochloride injection is supplied in sealed cartridges and poses no known environmental risk to healthcare providers. Accidental dermal exposure should be treated by removal of any contaminated clothing and rinsing the affected area with water.

Buprenorphine is a potent opioid and, like all drugs of this class, has been associated with abuse and dependence among healthcare providers. To control the risk of diversion, it is recommended that measures appropriate to the health care setting be taken to provide rigid accounting, control of wastage, and restriction of access.

Parenteral drug products should be inspected visually for particulate matter and discoloration prior to administration, whenever solution and container permit.

HOW SUPPLIED

Unit of Sale

Total Strength/ Total Volume (Concentration)

NDC 0409-2012-32

0.3 mg/mL

Box of 10

1 mL fill in 2.5 mL Carpuject™

Single-dose cartridge with Luer Lock for the Carpuject™ Syringe System

STORAGE AND HANDLING

Store at 20° to 25°C (68° to 77°F) [see USP Controlled Room Temperature].

Protect from prolonged exposure to light.

Retain in carton until time of use.

Do not freeze.

Carpuject™ Single-dose cartridges with Luer Lock are packaged in a Slim-Pak™ tamper detection package. Note that a needle is not included.

Instructions for Use of the Syringe Systems

Instructions for using the Carpuject™ Syringe are available with the reusable Carpuject™ Holder, List 2049-02.

Carpuject™ Single-dose cartridges are to be used ONLY with Carpuject™ Holders, List 2049-02.

Distributed by Hospira, Inc., Lake Forest, IL 60045 USA

LAB-0952-5.0

Revised: 12/2025

PRINCIPAL DISPLAY PANEL - 1 mL Cartridge Label

NDC 0409-2012-03

1 mL Single-dose Carpuject™
Sterile Cartridge Unit with Luer Lock
Buprenorphine
Hydrochloride Injection
CIII
Rx only
0.3 mg base/mL
For Intramuscular or Intravenous Use
PROTECT FROM LIGHT

PAA146018

Hospira

LOT #####AA
EXP DMMMYYYY

PRINCIPAL DISPLAY PANEL - 1 mL Cartridge Carton

NDC 0409-2012-32
Contains 10 of NDC 0409-2012-03
Rx only

1 mL Single-dose
10 Carpuject™
Sterile Cartridge Units
with Luer Lock

Needle not included

SLIM-PAK™
Tamper Detection Package

Buprenorphine
Hydrochloride
Injection
CIII

0.3 mg base/mL

For Intramuscular or
Intravenous Use

Carpuject Cartridges are
to be used ONLY with
Carpuject Holders.

Hospira